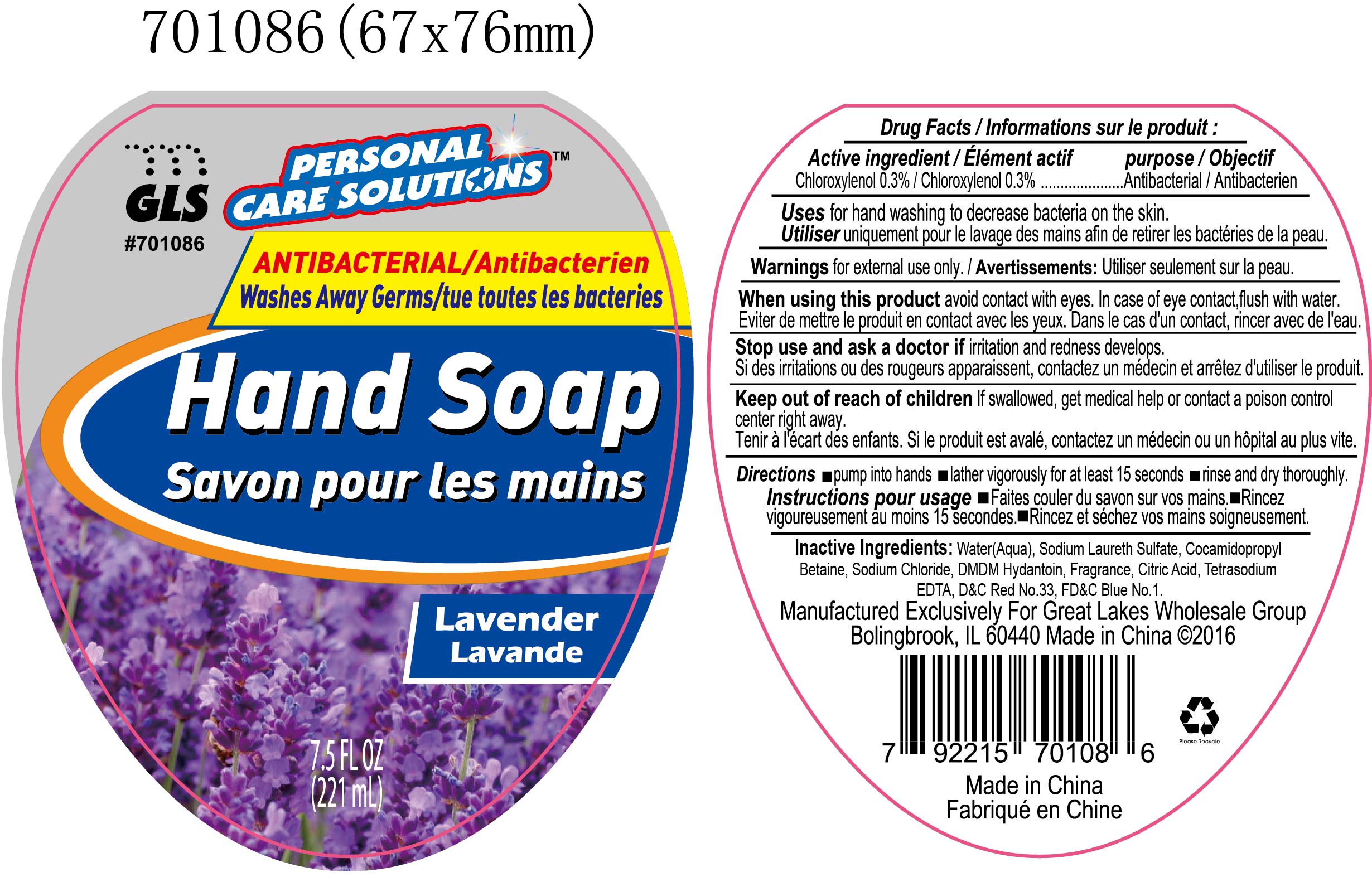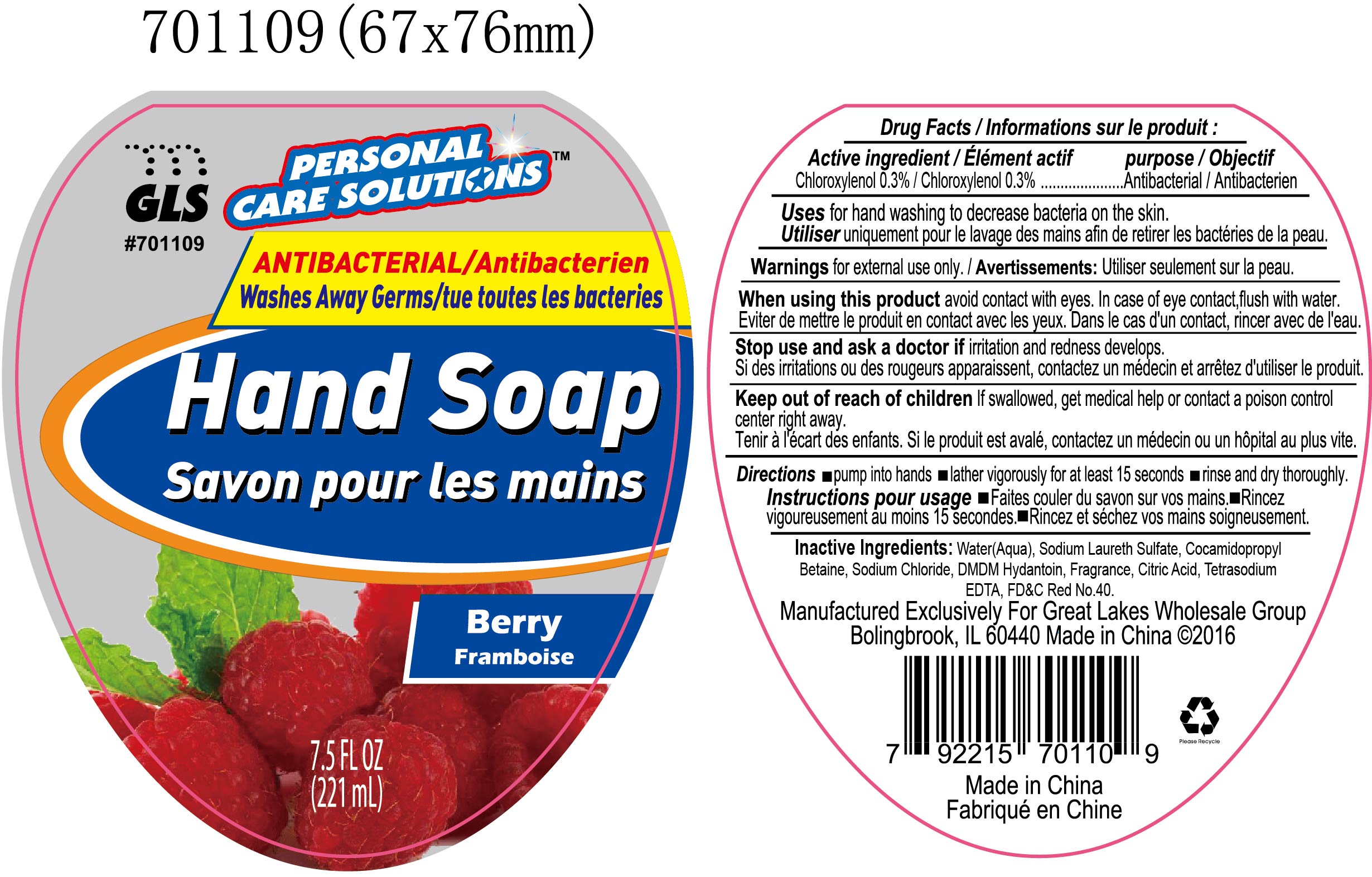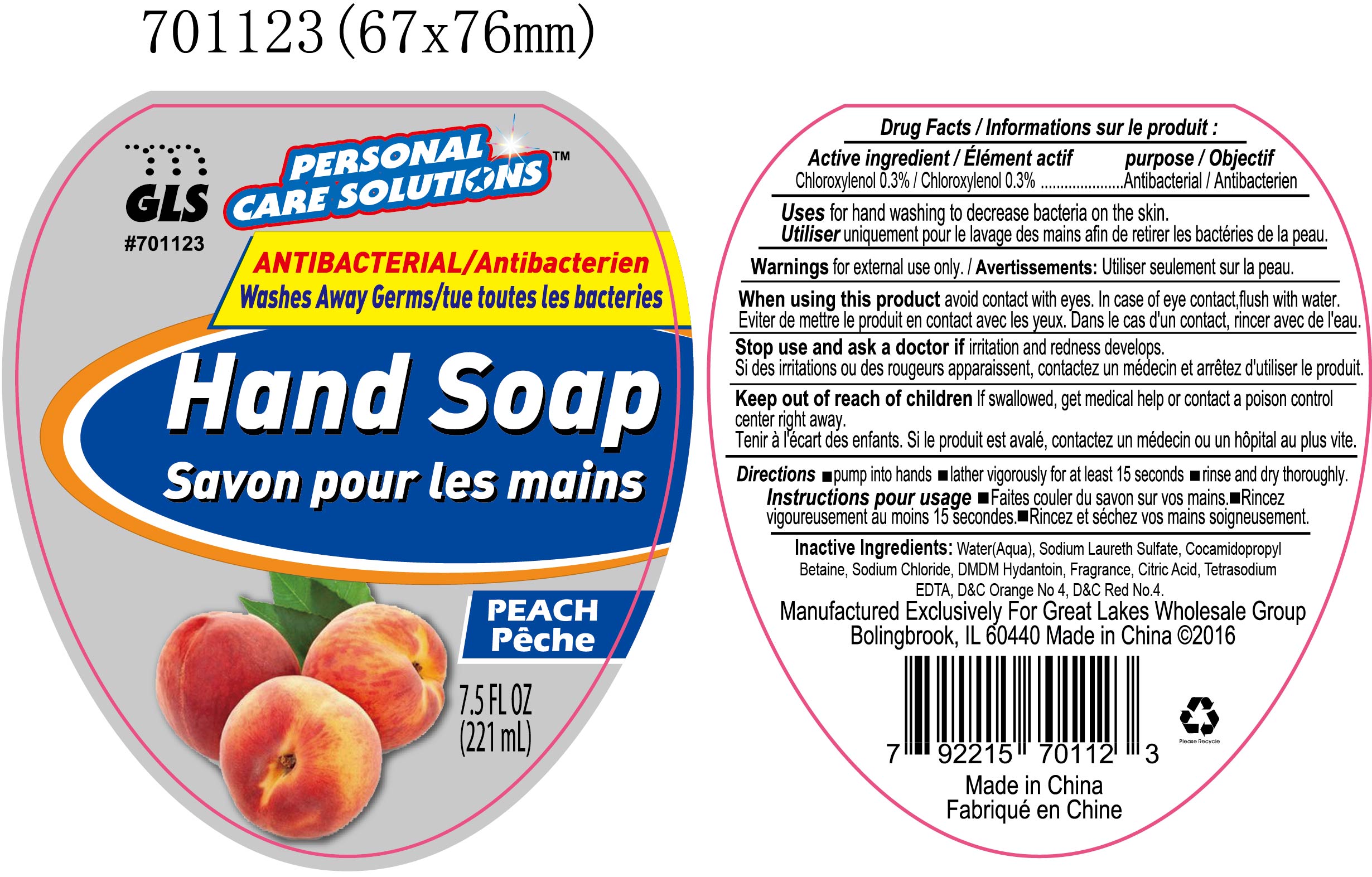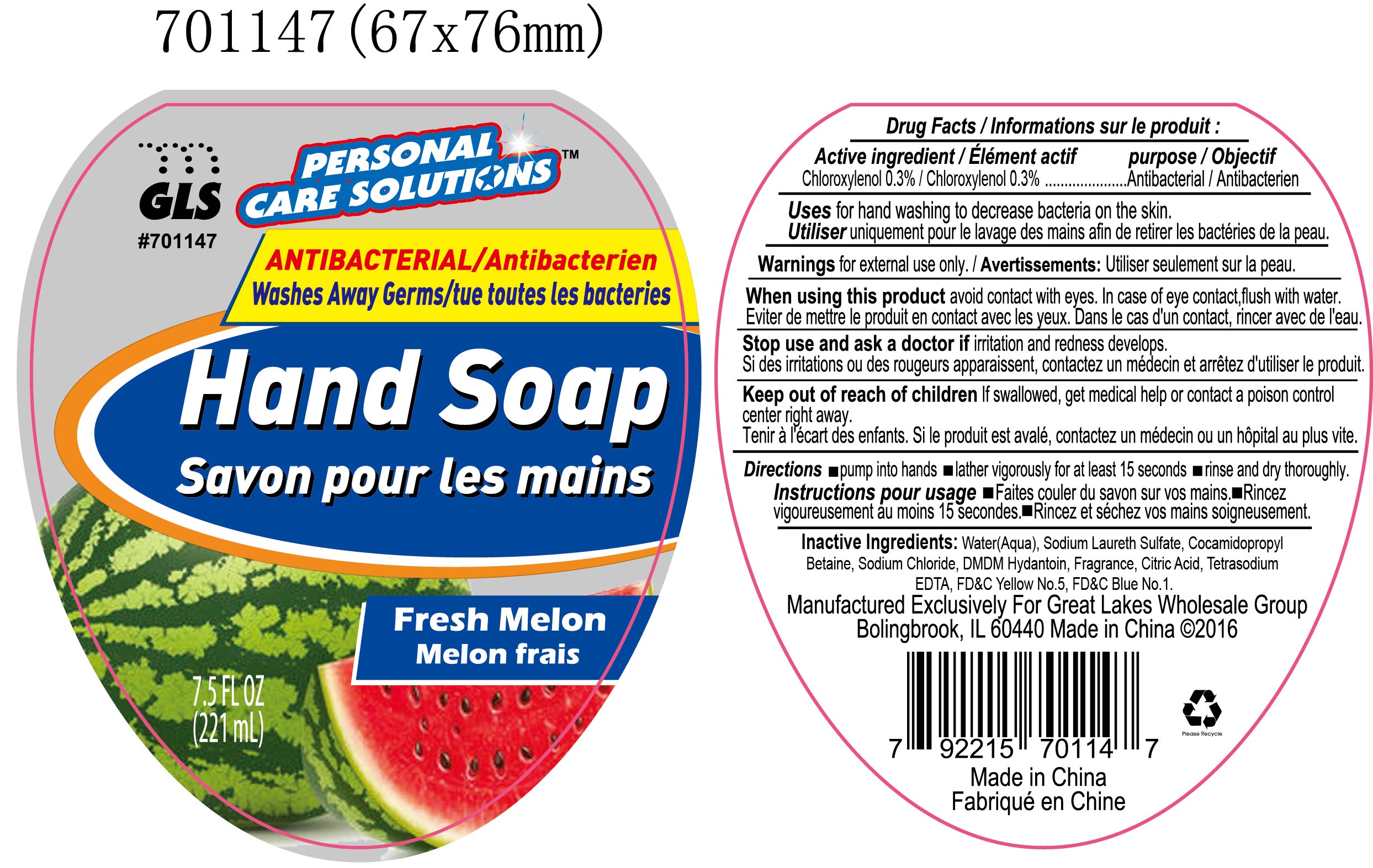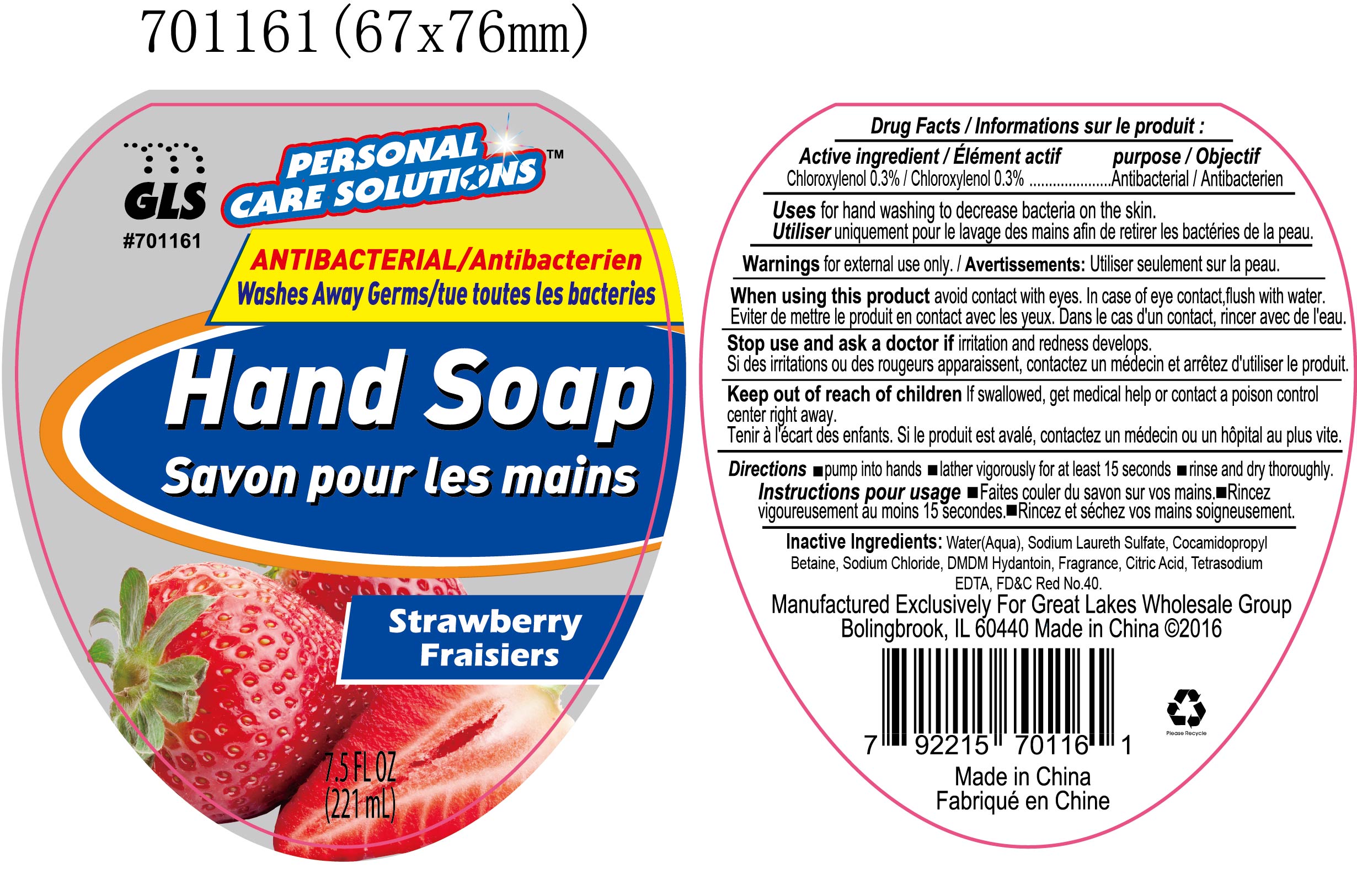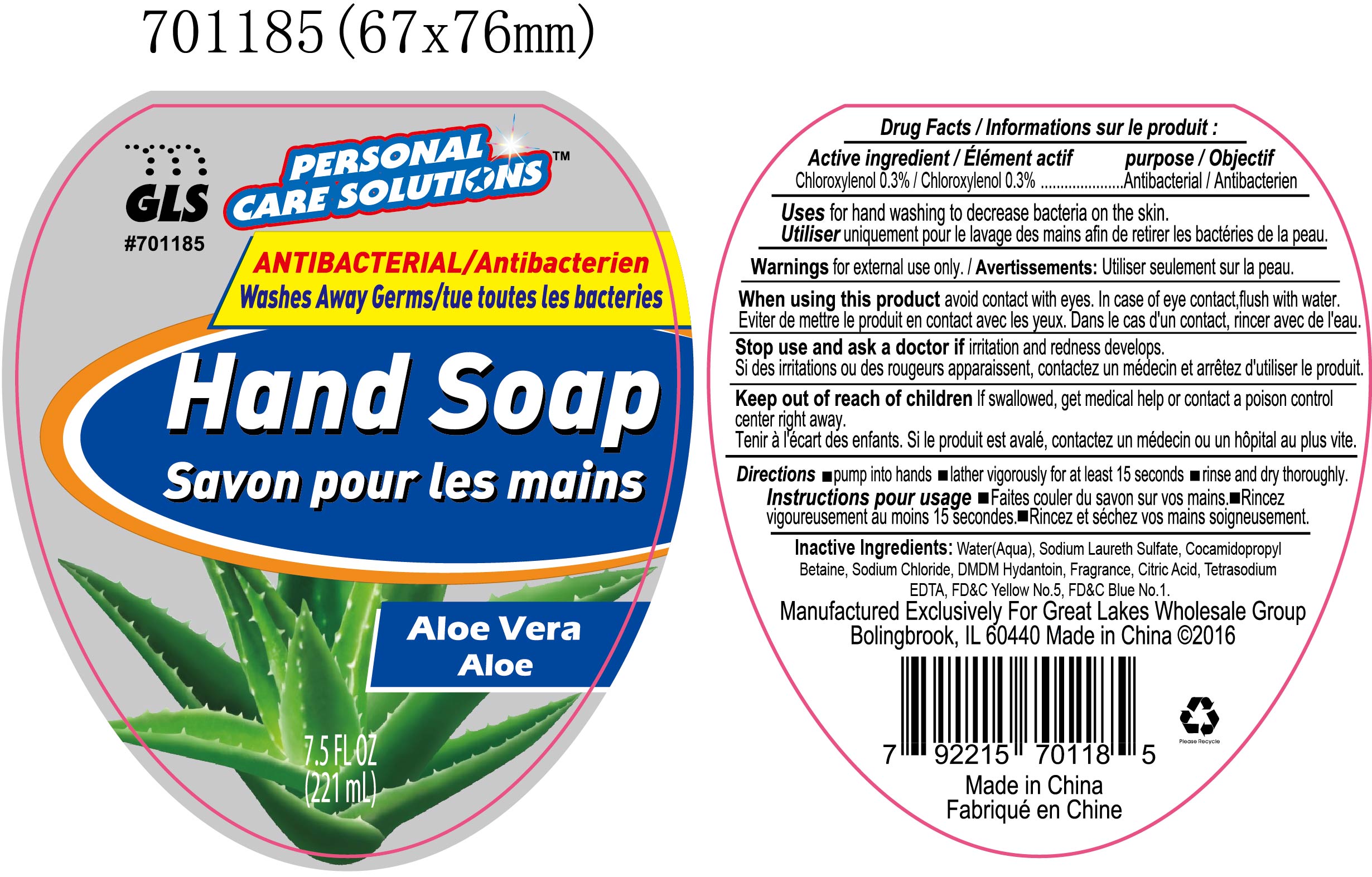 DRUG LABEL: health care personnel handwash
NDC: 64092-385 | Form: LIQUID
Manufacturer: Great Lakes Wholesale, Marketing, and Sales, Inc.
Category: otc | Type: HUMAN OTC DRUG LABEL
Date: 20161212

ACTIVE INGREDIENTS: CHLOROXYLENOL 0.663 g/221 mL
INACTIVE INGREDIENTS: WATER

DESCRIPTION

GLS PERSONAL CARE SOLUTIONS

Antibacterial Washes Away germs

Hand Soap

7.5 oz (221mL)

Lavender, Berry, Peach, Fresh Melon, Strawberry, or Aloe Vera

Active ingredient purpose

Chloroxylenol 0.3%..................................................Antibacterial

PURPOSE

Hand Soap

WARNINGS

For external use only.

When using this product avoid contact with eyes. In case of eye contact, flush with water.

Stop use and ask a doctor if irritation and redness develops.

KEEP OUT OF REACH OF CHILDREN

If swallowed, get medical hep or contact a poison control center right away.

INSTRUCTIONS FOR USE

- Pump into hands
- Lather vigorously for at least 15 seconds
- Rinse and dry thoroughly

INACTIVE INGREDIENT

Lavender NDC 64092-386-07

Water (aqua), ammonium lauryl sulfate, Cocamidopropyl Betaine, Sodium Chloride, DMDM Hydantoin, Fragrance, Citric Acid, Tetrasodium EDTA, D&C Red No.33, FD&C Blue No. 1.

Berry NDC 64092-309-07

Water (aqua), ammonium lauryl sulfate, Cocamidopropyl Betaine, Sodium Chloride, DMDM Hydantoin, Fragrance, Citric Acid, Tetrasodium EDTA, FD&C Red No.40.

Peach NDC 64092-323-07

Water (aqua), ammonium lauryl sulfate, Cocamidopropyl Betaine, Sodium Chloride, DMDM Hydantoin, Fragrance, Citric Acid, Tetrasodium EDTA, D&C Orange No.4, D&C Red No. 4.

Fresh Melon NDC 64092-347-07

Water (aqua), ammonium lauryl sulfate, Cocamidopropyl Betaine, Sodium Chloride, DMDM Hydantoin, Fragrance, Citric Acid, Tetrasodium EDTA, FD&C Yellow No. 5, FD&C Blue No. 1.

Strawberry NDC 64092-361-07

Water (aqua), ammonium lauryl sulfate, Cocamidopropyl Betaine, Sodium Chloride, DMDM Hydantoin, Fragrance, Citric Acid, Tetrasodium EDTA, FD&C Red No. 40.

Aloe Vera NDC 64092-385-07

Water (aqua), ammonium lauryl sulfate, Cocamidopropyl Betaine, Sodium Chloride, DMDM Hydantoin, Fragrance, Citric Acid, Tetrasodium EDTA, FD&C Yellow No. 5, FD&C Blue No. 1.

INDICATIONS AND USAGE

For hand washing to decrease bacteria on the skin

DOSAGE AND ADMINISTRATION

Antibacterial Hand soap

0.3% Chloroxylenol